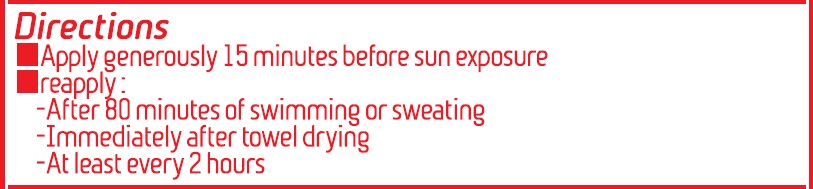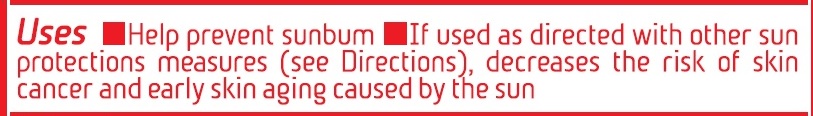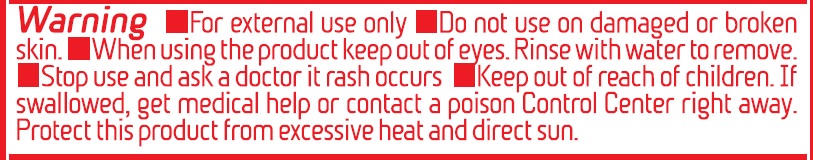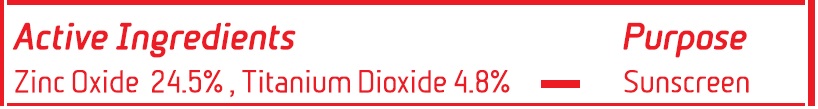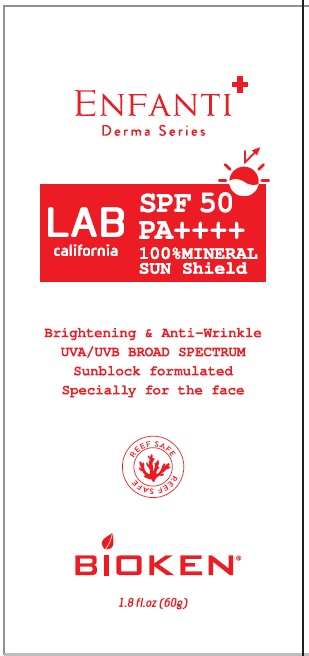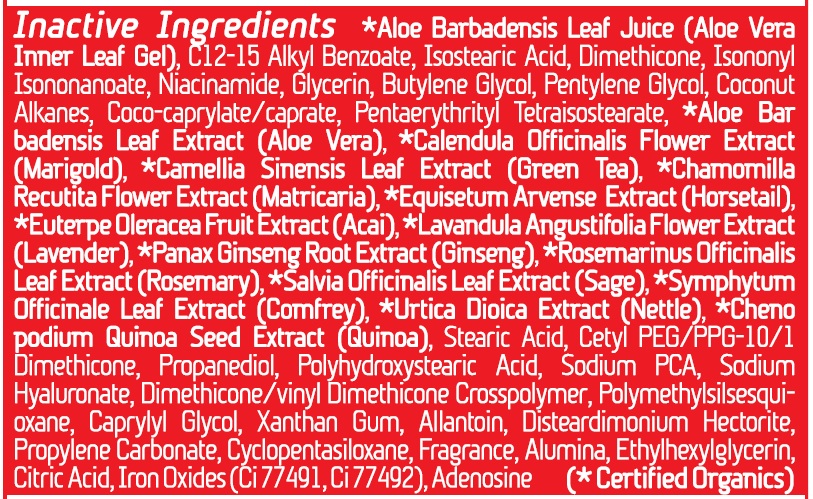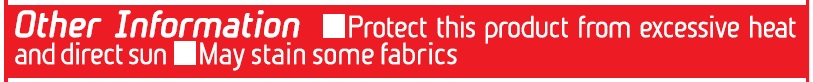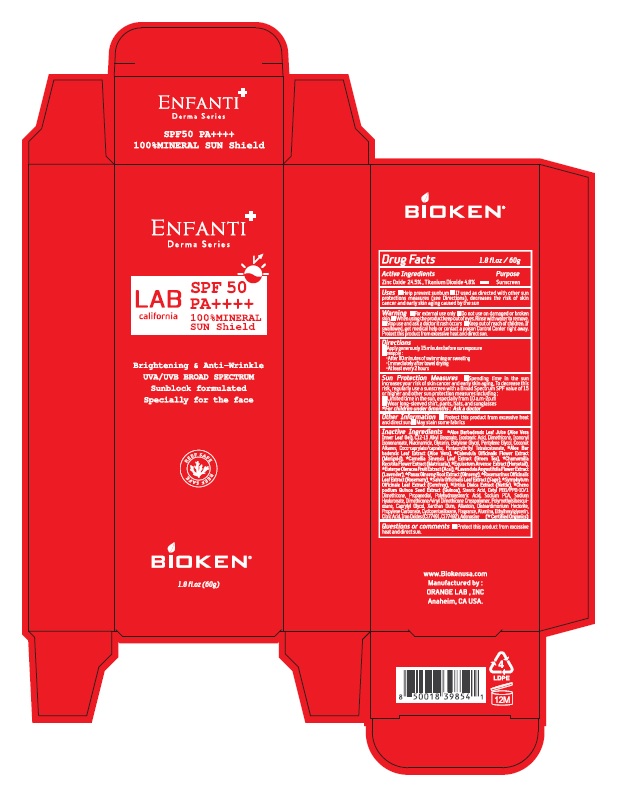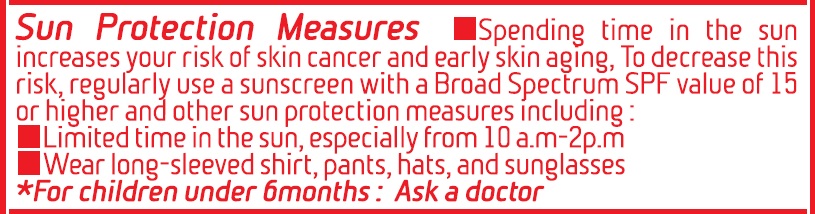 DRUG LABEL: Enfanti Derma Series 100% Mineral Sun Shield
NDC: 71331-110 | Form: CREAM
Manufacturer: Orange Lab
Category: otc | Type: HUMAN OTC DRUG LABEL
Date: 20230110

ACTIVE INGREDIENTS: TITANIUM DIOXIDE 2.88 g/60 g; ZINC OXIDE 14.7 g/60 g
INACTIVE INGREDIENTS: ANHYDROUS CITRIC ACID; FERRIC OXIDE RED; GLYCERIN; PENTYLENE GLYCOL; ALLANTOIN; ROSEMARY; ALKYL (C12-15) BENZOATE; CYCLOMETHICONE 5; SYMPHYTUM OFFICINALE WHOLE; CHENOPODIUM QUINOA SEED; POLYHYDROXYSTEARIC ACID (2300 MW); CAPRYLYL GLYCOL; ALOE VERA LEAF; COCO-CAPRYLATE/CAPRATE; MATRICARIA CHAMOMILLA LEAF; BUTYLENE GLYCOL; FERRIC OXIDE YELLOW; DISTEARDIMONIUM HECTORITE; PROPYLENE CARBONATE; EUTERPE OLERACEA WHOLE; PANAX GINSENG ROOT OIL; ALUMINUM OXIDE; EQUISETUM ARVENSE BRANCH; ISONONYL ISONONANOATE; SALVIA OFFICINALIS WHOLE; PENTAERYTHRITYL TETRAISOSTEARATE; URTICA DIOICA LEAF; ETHYLHEXYLGLYCERIN; DIMETHICONE 20; SODIUM PYRROLIDONE CARBOXYLATE; PROPANEDIOL; NIACINAMIDE; COCONUT ALKANES; LAVANDULA ANGUSTIFOLIA FLOWER; CAMELLIA SINENSIS FLOWER; HYALURONATE SODIUM; ADENOSINE; CALENDULA OFFICINALIS FLOWER; ISOSTEARIC ACID; STEARIC ACID; POLYMETHYLSILSESQUIOXANE (11 MICRONS); XANTHAN GUM; CETYL PEG/PPG-10/1 DIMETHICONE (HLB 2); DIMETHICONE/VINYL DIMETHICONE CROSSPOLYMER (SOFT PARTICLE)

Enfanti Derma Series SPF 50 PA++++ 1.8 fl oz.